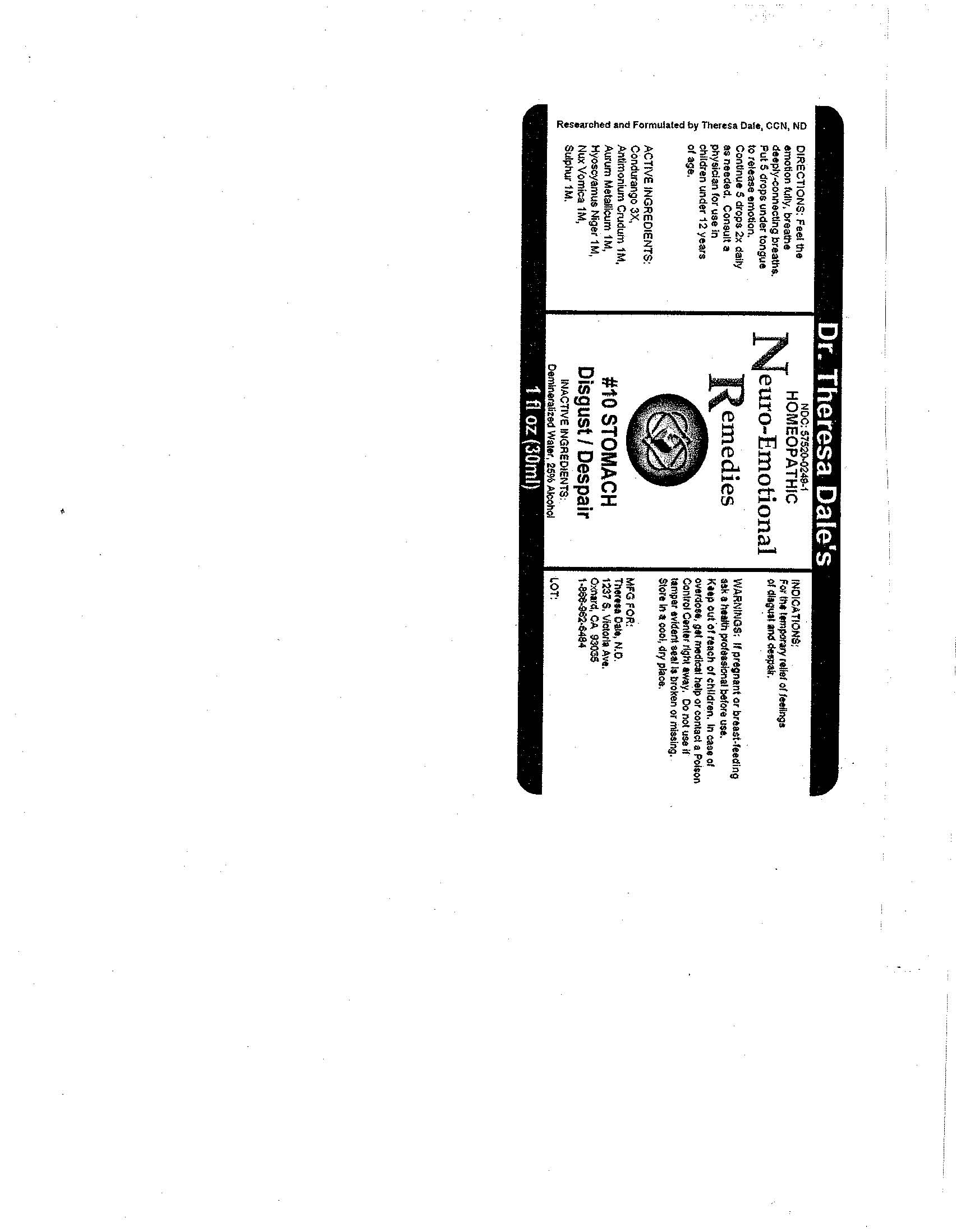 DRUG LABEL: 10 Stomach
NDC: 57520-0249 | Form: LIQUID
Manufacturer: Apotheca Company
Category: homeopathic | Type: HUMAN OTC DRUG LABEL
Date: 20100803

ACTIVE INGREDIENTS: ANTIMONY TRISULFIDE 1 [hp_M]/1 mL; GOLD 1 [hp_M]/1 mL; HYOSCYAMUS NIGER 1 [hp_M]/1 mL; STRYCHNOS NUX-VOMICA SEED 1 [hp_M]/1 mL; SULFUR 1 [hp_M]/1 mL; MARSDENIA CONDURANGO BARK     3 [hp_X]/1 mL
INACTIVE INGREDIENTS: WATER; ALCOHOL

#10 Stomach

ACTIVE INGREDIENT

ACTIVE INGREDIENTS: Condurango 3X, Antimonium crudum 1M, Aurum metallicum 1M, Hyoscyamus niger 1M, Nux vomica 1M, Sulphur 1M.

PURPOSE

INDICATIONS: For the temporary relief of feelings of disgust and despair.

WARNINGS

WARNINGS: If pregnant or breast-feeding, ask a health professional before use.

Keep out of reach of children. In case of overdose, get medical help or contact a Poison Control Center right away.

Do not use if tamper evident seal is broken or missing. Store in a cool, dry place.

DOSAGE AND ADMINISTRATION

DIRECTIONS: Feel the emotion fully, breathe deeply-connected breaths. Put 5 drops under tongue to release emotion. Continue 5 drops 2x daily as needed. Consult a physician for use in children under 12 years of age.

INACTIVE INGREDIENTS: Demineralized water, 25% Alcohol.

KEEP OUT OF REACH OF CHILDREN. In case of overdose, get medical help or contact a Poison Control Center right away.

INDICATIONS AND USAGE

INDICATIONS: For the temporary relief of feelings of disgust and despair.

QUESTIONS

MFG. FOR:

Theresa Dale, N.D.

1237 S. Victoria Ave.

Oxnard, CA 93035

1-886-962-6484

PACKAGE LABEL

Dr. Theresa Dale's

NDC: 57520-0249-1

HOMEOPATHIC

Neuro-Emotional Remedies

#10 STOMACH

Disgust/Despair

1 fl oz (30 ml)